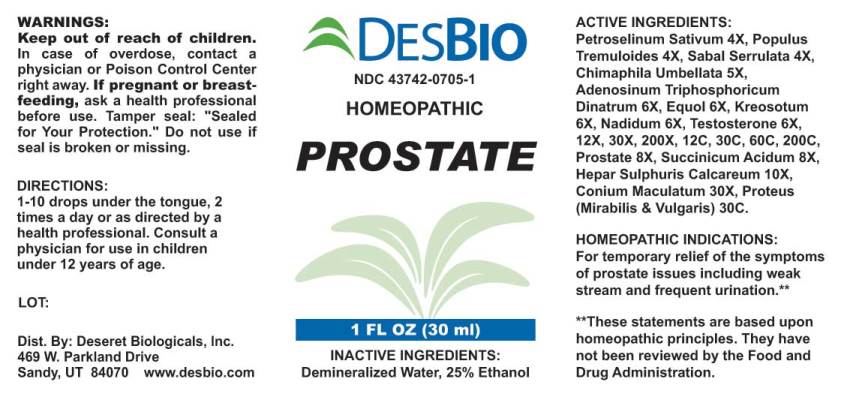 DRUG LABEL: Prostate
NDC: 43742-0705 | Form: LIQUID
Manufacturer: Deseret Biologicals, Inc.
Category: homeopathic | Type: HUMAN OTC DRUG LABEL
Date: 20231012
DEA Schedule: CIII

ACTIVE INGREDIENTS: PETROSELINUM CRISPUM 4 [hp_X]/1 mL; POPULUS TREMULOIDES BARK 4 [hp_X]/1 mL; POPULUS TREMULOIDES LEAF 4 [hp_X]/1 mL; SAW PALMETTO 4 [hp_X]/1 mL; CHIMAPHILA UMBELLATA 5 [hp_X]/1 mL; ADENOSINE TRIPHOSPHATE DISODIUM 6 [hp_X]/1 mL; EQUOL, (+/-)- 6 [hp_X]/1 mL; WOOD CREOSOTE 6 [hp_X]/1 mL; NADIDE 6 [hp_X]/1 mL; TESTOSTERONE 6 [hp_X]/1 mL; SUS SCROFA PROSTATE 8 [hp_X]/1 mL; SUCCINIC ACID 8 [hp_X]/1 mL; CALCIUM SULFIDE 10 [hp_X]/1 mL; CONIUM MACULATUM FLOWERING TOP 30 [hp_X]/1 mL; PROTEUS MIRABILIS 30 [hp_C]/1 mL; PROTEUS VULGARIS 30 [hp_C]/1 mL
INACTIVE INGREDIENTS: WATER; ALCOHOL

Drug Facts:

ACTIVE INGREDIENTS:

Petroselinum Sativum 4X, Populus Tremuloides 4X, Sabal Serrulata 4X, Chimaphila Umbellata 5X, Adenosinum Triphosphoricum Dinatrum 6X, Equol 6X, Kreosotum 6X, Nadidum 6X, Testosterone 6X, 12X, 30X, 200X, 12C, 30C, 60C, 200C, Prostate (Suis) 8X, Succinicum Acidum 8X, Hepar Sulphuris Calcareum 10X, Conium Maculatum 30X, Proteus (Mirabilis) 30C, Proteus (Vulgaris) 30C.

HOMEOPATHIC INDICATIONS:

For temporary relief of the symptoms of prostate issues including weak stream and frequent urination.**

**These statements are based upon homeopathic principles. They have not been reviewed by the Food and Drug Administration.

WARNINGS:

Keep out of reach of children. In case of overdose, contact physician or Poison Control Center right away.

If pregnant or breast-feeding, ask a health professional before use.

Tamper seal: "Sealed for Your Protection." Do not use if seal is broken or missing.

Keep out of reach of children. In case of overdose, contact physician or Poison Control Center right away.

DIRECTIONS:

1-10 drops under the tongue, 2 times a day or as directed by a health professional. Consult a physician for use in children under 12 years of age.

HOMEOPATHIC INDICATIONS:

For temporary relief of the symptoms of prostate issues including weak stream and frequent urination.**

**These statements are based upon homeopathic principles. They have not been reviewed by the Food and Drug Administration.

INACTIVE INGREDIENTS:

Demineralized water, 25% Ethanol.

QUESTIONS:

Dist. By: Deseret Biologicals, Inc.

469 W. Parkland Drive

Sandy, UT 84070 www.desbio.com

PACKAGE LABEL DISPLAY:

DESBIO

NDC 43742-0705-1

HOMEOPATHIC

PROSTATE

1 FL OZ (30 ml)